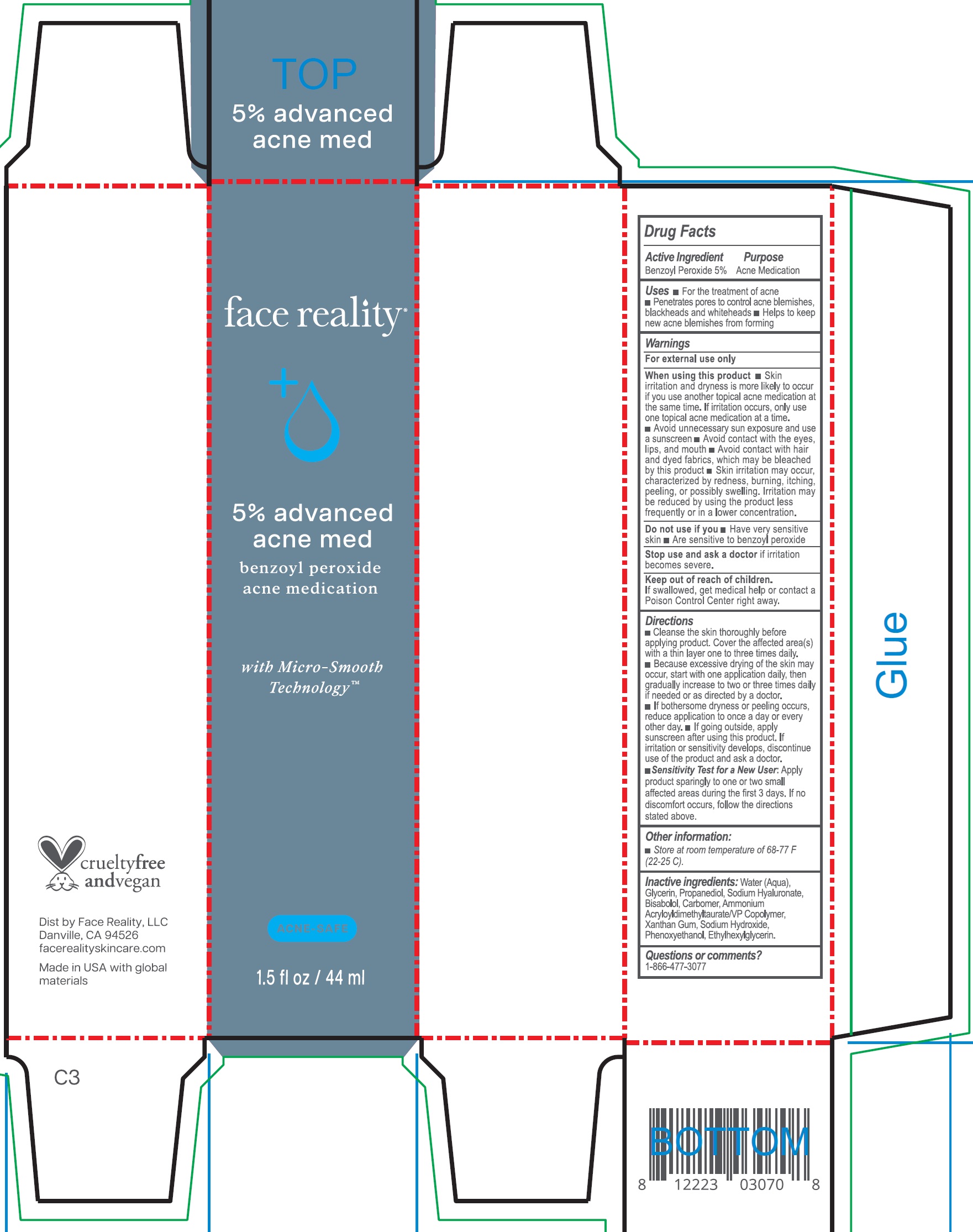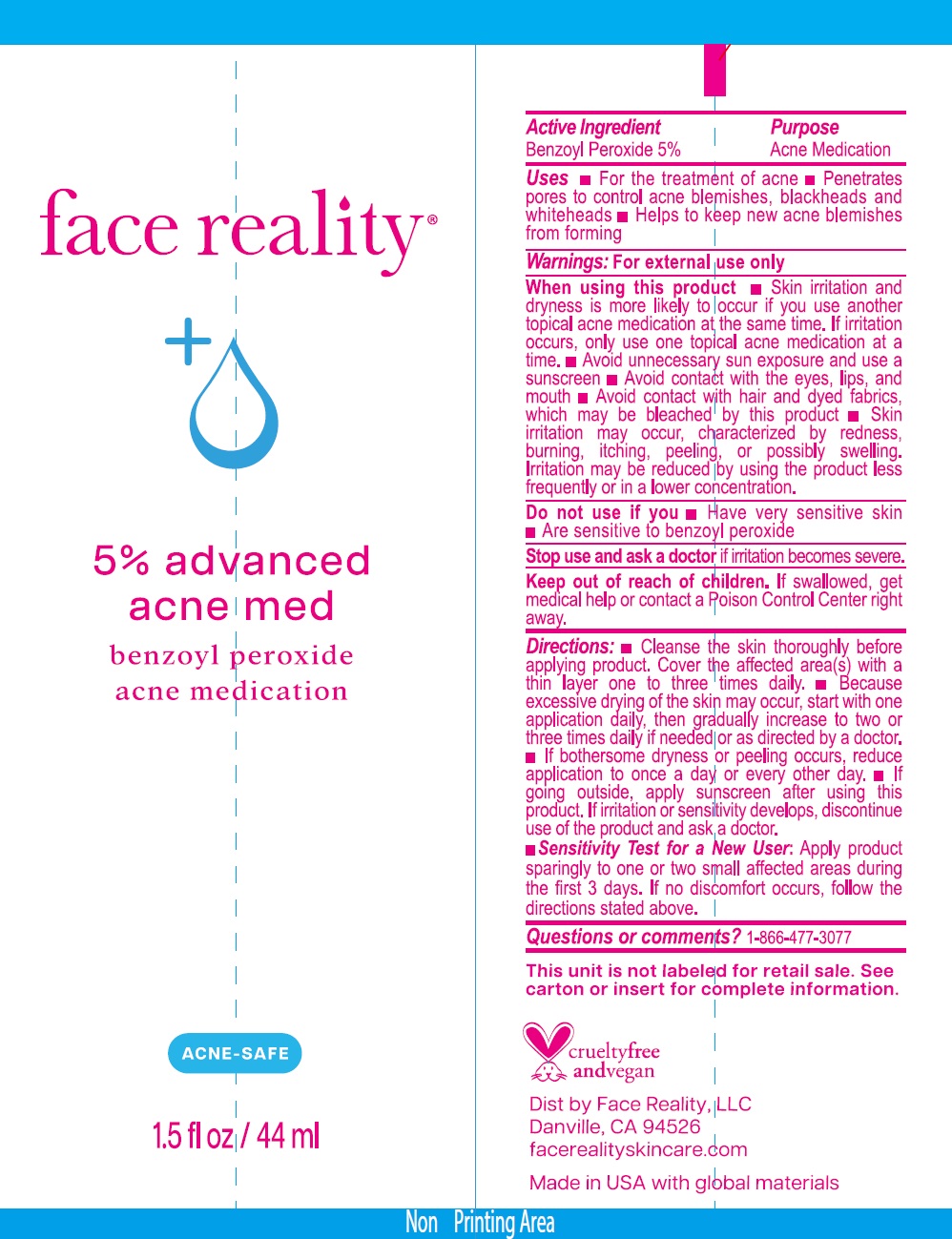 DRUG LABEL: Face Reality 5% Advanced Acne Med
NDC: 70707-157 | Form: CREAM
Manufacturer: Face Reality
Category: otc | Type: HUMAN OTC DRUG LABEL
Date: 20240726

ACTIVE INGREDIENTS: BENZOYL PEROXIDE 50 mg/1 mL
INACTIVE INGREDIENTS: WATER; GLYCERIN; PROPANEDIOL; HYALURONATE SODIUM; LEVOMENOL; CARBOMER HOMOPOLYMER, UNSPECIFIED TYPE; AMMONIUM ACRYLOYLDIMETHYLTAURATE/VP COPOLYMER; XANTHAN GUM; SODIUM HYDROXIDE; PHENOXYETHANOL; ETHYLHEXYLGLYCERIN

Face Reality 5% Advanced Acne Med

Active Ingredient

Benzoyl Peroxide 5%

Purpose

Acne Medication

Uses

- For the treatment of acne
- Penetrates pores to control acne blemishes, blackheads and whiteheads
- Helps to keep new acne blemishes from forming

Warnings

For external use only

When using this product

- Skin irritation and dryness is more likely to occur if you use another topical acne medication at the same time. If irritation occurs, only use one topical acne medication at a time.
- Avoid unnecessary sun exposure and use a sunscreen
- Avoid contact with the eyes, lips, and mouth
- Avoid contact with hair and dyed fabrics, which may be bleached by this product
- Skin irritation may occur, characterized by redness, burning, itching, peeling, or possibly swelling. Irritation may be reduced by using the product less frequently or in a lower concentration.

Do not use if you

- Have very sensitive skin
- Are sensitive to benzoyl peroxide

Stop use and ask a doctor

if irritation becomes severe.

Keep out of reach of children.

If swallowed, get medical help or contact a Poison Control Center right away.

Directions

- Cleanse the skin thoroughly before applying product. Cover the affected area(s) with a thin layer one to three times daily.
- Because excessive drying of the skin may occur, start with one application daily, then gradually increase to two or three times daily if needed or as directed by a doctor.
- If bothersome dryness or peeling occurs, reduce application to once a day or every other day.
- If going outside, apply sunscreen after using this product. If irritation or sensitivity develops, discontinue use of the product and ask a doctor.
- Sensitivity Test for a New User:Apply product sparingly to one or two small affected areas during the first 3 days. If no discomfort occurs, follow the directions stated above.

Other information:

- Store at room temperature of 68-77 F (22-25 C).

Inactive ingredients:

Water (Aqua), Glycerin, Propanediol, Sodium Hyaluronate, Bisabolol, Carbomer, Ammonium Acryloyldimethyltaurate/VP Copolymer, Xanthan Gum, Sodium Hydroxide, Phenoxyethanol, Ethylhexylglycerin.

Questions or comments?

1-866-477-3077